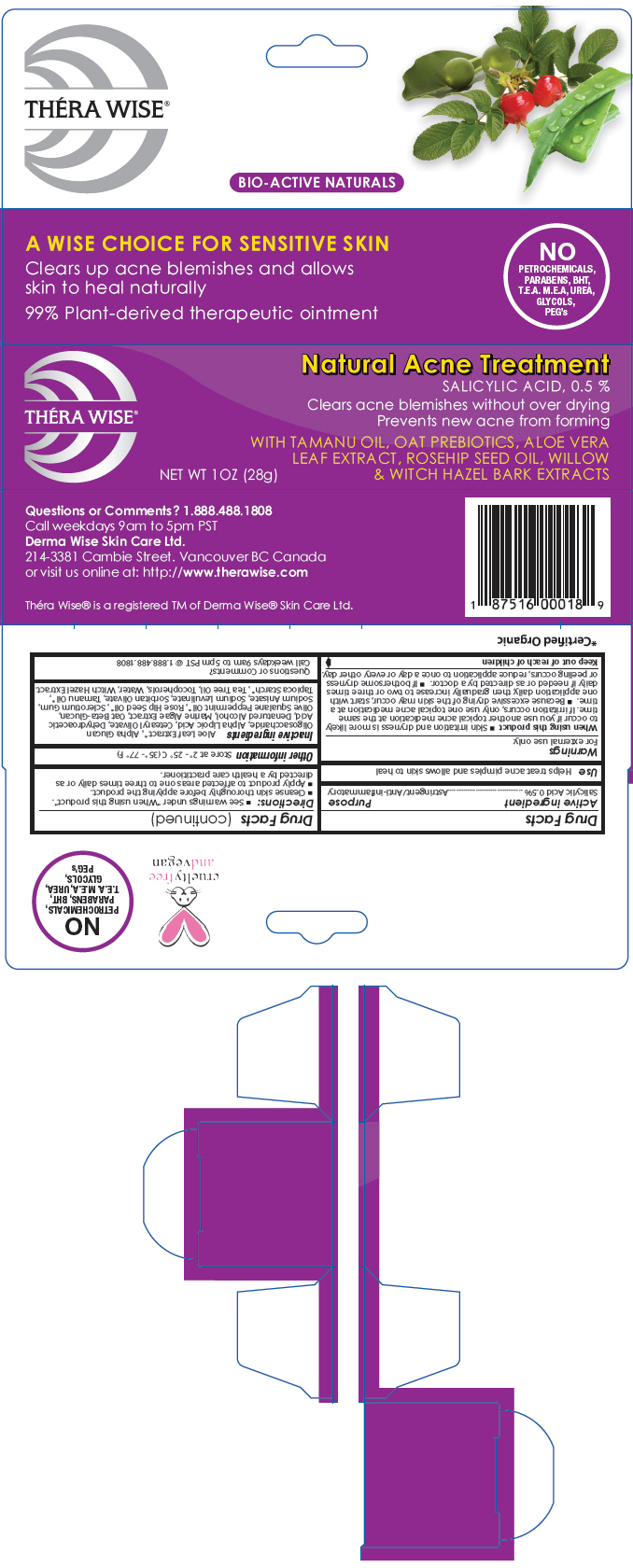 DRUG LABEL: Thera Wise Natural Acne
NDC: 43347-189 | Form: OINTMENT
Manufacturer: Derma Wise Skin Care Ltd.
Category: otc | Type: HUMAN OTC DRUG LABEL
Date: 20220119

ACTIVE INGREDIENTS: Salicylic Acid 0.14 g/28 g
INACTIVE INGREDIENTS: Aloe Vera Leaf; .Alpha.-Glucan Oligosaccharide; ALPHA LIPOIC ACID; Alcohol; Squalane; Peppermint Oil; Rosa Moschata Oil; Betasizofiran; Sodium Anisate; Sodium Levulinate; Sorbitan Olivate; Tamanu Oil; Starch, Tapioca; Tea Tree Oil; Tocopherol; Water; Hamamelis Virginiana Top; Nori

Théra Wise® Natural Acne

Drug Facts

Active ingredient

Salicylic Acid 0.5%

Purpose

Astringent/Anti-inflammatory

Use

Helps treat acne pimples and allows skin to heal

Warnings

For external use only.

When using this product

- Skin irritation and dryness is more likely to occur if you use another topical acne medication at the same time. If irritation occurs, only use one topical acne medication at a time.
- Because excessive drying of the skin may occur, start with one application daily, then gradually increase to two or three times daily if needed or as directed by a doctor.
- If bothersome dryness or peeling occurs, reduce application to once a day or every other day.

Keep out of reach of children

Directions

- See warnings under "When using this product".
- Cleanse skin thoroughly before applying the product.
- Apply product to affected areas one to three times daily or as directed by a health care practitioner.

Other information

Store at 2°- 25° C (35°- 77° F)

Inactive ingredients

Aloe Leaf Extract [Certified Organic] , Alpha Glucan Oligosaccharide, Alpha Lipoic Acid, Cetearyl Olivate, Dehydroacetic Acid, Denatured Alcohol, Marine Algae Extract, Oat Beta-Glucan, Olive Squalane Peppermint Oil, Rose Hip Seed Oil, Sclerotium Gum, Sodium Anisate, Sodium Levulinate, Sorbitan Olivate, Tamanu Oil, Tapioca Starch, Tea Tree Oil, Tocopherols, Water, Witch Hazel Extract.

Questions or Comments?

Call weekdays 9am to 5pm PST @ 1.888.488.1808

PRINCIPAL DISPLAY PANEL - 28 g Tube Box

THÉRA WISE®

Natural Acne Treatment
SALICYLIC ACID, 0.5 %
Clears acne blemishes without over drying
Prevents new acne from forming

WITH TAMANU OIL, OAT PREBIOTICS, ALOE VERA
LEAF EXTRACT, ROSEHIP SEED OIL, WILLOW
& WITCH HAZEL BARK EXTRACTS

NET WT 1OZ (28g)